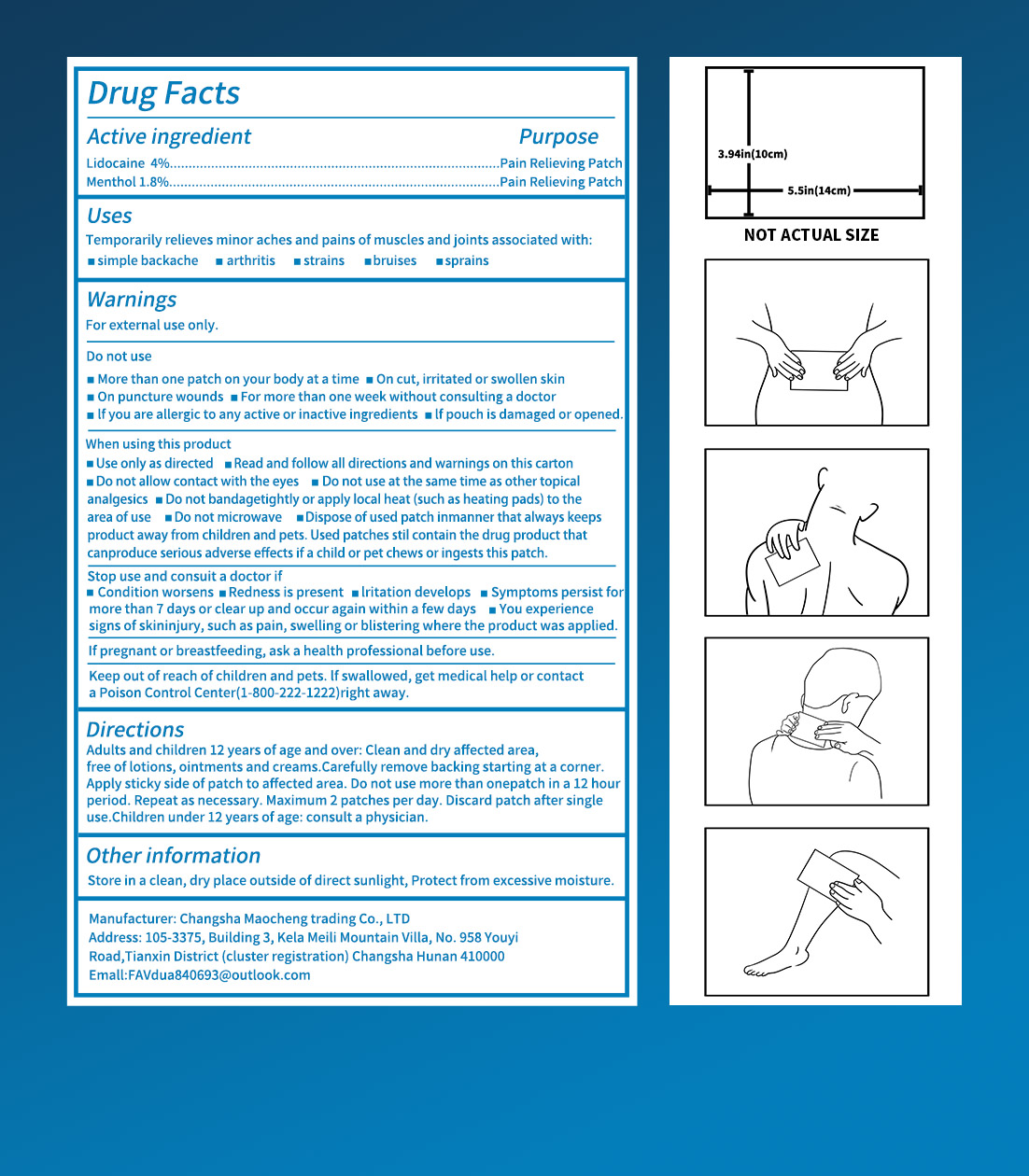 DRUG LABEL: lidocaine pain relief patches
NDC: 84876-101 | Form: PATCH
Manufacturer: Changsha Maocheng Trading Co., Ltd
Category: otc | Type: HUMAN OTC DRUG LABEL
Date: 20250728

ACTIVE INGREDIENTS: MENTHOL 1.8 g/100 g; LIDOCAINE 5 g/100 g
INACTIVE INGREDIENTS: SODIUM POLYACRYLATE (2500000 MW); WATER; POLYVINYL ALCOHOL; GLYCERIN; ALUMINUM ZIRCONIUM TRICHLOROHYDREX GLY; EDETATE DISODIUM; TARTARIC ACID; GLUCOSAMINE

ACTIVE INGREDIENT

Lidocaine 4%

Menthol 1.8%

INACTIVE INGREDIENT

Purified water
g1 ycerol
Glucosamine
polyving akohol
Tartaric acid
Disodium edetate dihydrate
Aluminium glycinat
Sodium polyacrylate

PURPOSE

Temporarily relieves minor aches and pains of muscles and joints associated with:
msimple backache marthritis mstrains mbruises msprains

WARNINGS

WarningsFor external use only.

Keep out of reach of children and pets. lf swallowed, get medical help or contacta Poison Control Center(1-800-222-1222)right away.

Directions
Adults and children 12 years of age and over: Clean and dry affected area,free of lotions, ointments and creams.Carefully remove backing starting at a corner.Apply sticky side of patch to affected area. Do not use more than onepatch in a 12 hourperiod. Repeat as necessary. Maximum 2 patches per day. Discard patch after singleuse.Children under 12 years of age: consult a physician.

DOSAGE AND ADMINISTRATION

Maximum 2 patches per day. Discard patch after singleuse.Children under 12 years of age: consult a physician.

OTHER SAFETY INFORMATION

Otherinformation
Store in a clean, dry place outside of direct sunlight, Protect from excessive moisture.